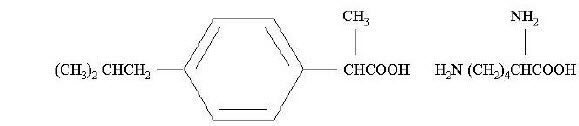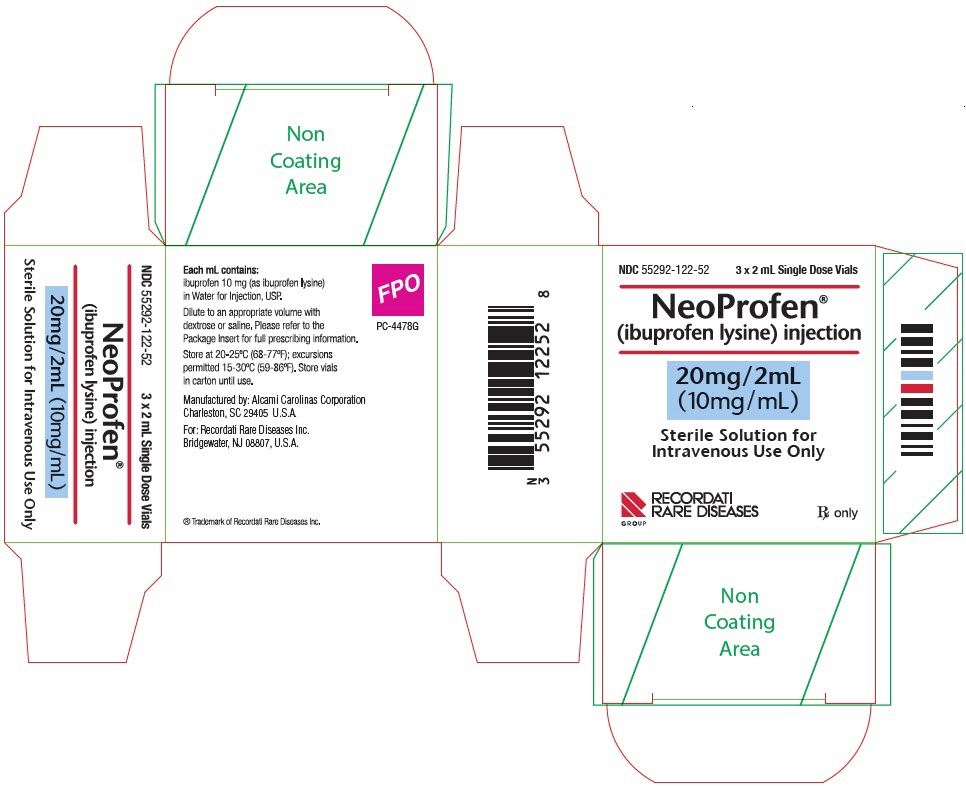 DRUG LABEL: NEOPROFEN
NDC: 55292-122 | Form: SOLUTION
Manufacturer: Recordati Rare Diseases Inc.
Category: prescription | Type: HUMAN PRESCRIPTION DRUG LABEL
Date: 20241015

ACTIVE INGREDIENTS: ibuprofen lysine 10 mg/1 mL
INACTIVE INGREDIENTS: water

HIGHLIGHTS OF PRESCRIBING INFORMATION

These highlights do not include all the information needed to use NEOPROFEN safely and effectively. See full prescribing information for NEOPROFEN.
NEOPROFEN® (ibuprofen lysine) Injection, for intravenous use
Initial U.S. Approval: 1974

RECENT MAJOR CHANGES

Warnings and Precautions (5.6) | 10/2023

1 INDICATIONS AND USAGE

NeoProfen is a nonsteroidal anti-inflammatory drug indicated to close a clinically significant patent ductus arteriosus (PDA) in premature infants weighing between 500 and 1500 g, who are no more than 32 weeks gestational age when usual medical management is ineffective. The clinical trial was conducted among infants with an asymptomatic PDA. However, the consequences beyond 8 weeks after treatment have not been evaluated; therefore, treatment should be reserved for infants with clear evidence of a clinically significant PDA. (1)

2 DOSAGE AND ADMINISTRATION

- A course of therapy is three doses administered I.V. (2.1)
- An initial dose of 10 mg/kg (based on birth weight) is followed by two doses of 5 mg/kg each, after 24 and 48 hours (2.1)
- Do not administer if anuria or marked oliguria (<0.6 mL/kg/hr) is evident at the scheduled time of the second or third dose (2.1)

3 DOSAGE FORMS AND STRENGTHS

- 20 mg/2 mL (10 mg/mL) as a clear sterile preservative-free solution of the L-lysine salt of ibuprofen in a 2 mL single-use vial (3)

4 CONTRAINDICATIONS

NeoProfen is contraindicated in preterm infants:

- With proven or suspected infection that is untreated (4)
- With congenital heart disease in whom patency of the PDA is necessary for satisfactory pulmonary or systemic blood flow (4)
- With impaired renal function (4)
- With thrombocytopenia, coagulation defects or who are bleeding (4)
- With or who are suspected of having necrotizing enterocolitis (4)

5 WARNINGS AND PRECAUTIONS

- NeoProfen has not been assessed for neurodevelopmental outcome and growth (5.1)
- NeoProfen may alter the usual signs of infection (5.2)
- NeoProfen can inhibit platelet aggregation, and has been shown to prolong bleeding time in normal adult subjects (5.3)
- Ibuprofen has been shown to displace bilirubin from albumin binding-sites (5.4)
- NeoProfen should be administered carefully to avoid extravascular injection or leakage (5.5)
- NeoProfen may cause serious skin reactions (5.6)

6 ADVERSE REACTIONS

Most common adverse reactions (≥10%) are sepsis, anemia, intraventricular bleeding, apnea, gastrointestinal disorders, impaired renal function, respiratory infection, skin lesions, hypoglycemia, hypocalcemia, respiratory failure. (6)

To report SUSPECTED ADVERSE REACTIONS, contact Recordati Rare Diseases Inc. at 1-888-575-8344, or FDA at 1-800-FDA-1088 or www.fda.gov/medwatch.

7 DRUG INTERACTIONS

Diuretics: Increased risk of renal dysfunction. (7)

FULL PRESCRIBING INFORMATION

1 INDICATIONS AND USAGE

NeoProfen is indicated to close a clinically significant patent ductus arteriosus (PDA) in premature infants weighing between 500 and 1500 g, who are no more than 32 weeks gestational age when usual medical management (e.g., fluid restriction, diuretics, respiratory support, etc.) is ineffective. The clinical trial was conducted among infants with an asymptomatic PDA. However, the consequences beyond 8 weeks after treatment have not been evaluated; therefore, treatment should be reserved for infants with clear evidence of a clinically significant PDA.

2 DOSAGE AND ADMINISTRATION

2.1 Recommended Dose

A course of therapy is three doses of NeoProfen administered intravenously (administration via an umbilical arterial line has not been evaluated). An initial dose of 10 mg per kilogram is followed by two doses of 5 mg per kilogram each, after 24 and 48 hours. All doses should be based on birth weight. If anuria or marked oliguria (urinary output <0.6 mL/kg/hr) is evident at the scheduled time of the second or third dose of NeoProfen, no additional dosage should be given until laboratory studies indicate that renal function has returned to normal. If the ductus arteriosus closes or is significantly reduced in size after completion of the first course of NeoProfen, no further doses are necessary. If during continued medical management the ductus arteriosus fails to close or reopens, then a second course of NeoProfen, alternative pharmacological therapy, or surgery may be necessary.

2.2 Directions for Use

For intravenous administration only. Parenteral drug products should be inspected visually for particulate matter and discoloration prior to administration whenever solution and container permit. Do not use NeoProfen if particulate matter is observed.

After the first withdrawal from the vial, any solution remaining must be discarded because NeoProfen contains no preservative.

For administration, NeoProfen should be diluted to an appropriate volume with dextrose or saline. NeoProfen should be prepared for infusion and administered within 30 minutes of preparation and infused continuously over a period of 15 minutes. The drug should be administered via the IV port that is nearest the insertion site. After the first withdrawal from the vial, any solution remaining must be discarded because NeoProfen contains no preservative.

Since NeoProfen is potentially irritating to tissues, it should be administered carefully to avoid extravasation.

NeoProfen should not be simultaneously administered in the same intravenous line with Total Parenteral Nutrition (TPN). If necessary, TPN should be interrupted for a 15-minute period prior to and after drug administration. Line patency should be maintained by using dextrose or saline.

3 DOSAGE FORMS AND STRENGTHS

20 mg/2 mL (10 mg/mL) as a clear sterile preservative-free solution of the L-lysine salt of ibuprofen in a 2 mL single-use vial.

4 CONTRAINDICATIONS

NeoProfen is contraindicated in:

- Preterm infants with proven or suspected infection that is untreated;
- Preterm infants with congenital heart disease in whom patency of the PDA is necessary for satisfactory pulmonary or systemic blood flow (e.g., pulmonary atresia, severe tetralogy of Fallot, severe coarctation of the aorta);
- Preterm infants who are bleeding, especially those with active intracranial hemorrhage or gastrointestinal bleeding;
- Preterm infants with thrombocytopenia;
- Preterm infants with coagulation defects;
- Preterm infants with or who are suspected of having necrotizing enterocolitis;
- Preterm infants with significant impairment of renal function.

5 WARNINGS AND PRECAUTIONS

5.1 General

There are no long-term evaluations of the infants treated with ibuprofen at durations greater than the 36 weeks post-conceptual age observation period. Ibuprofen's effects on neurodevelopmental outcome and growth as well as disease processes associated with prematurity (such as retinopathy of prematurity and chronic lung disease) have not been assessed.

5.2 Infection

NeoProfen may alter the usual signs of infection. The physician must be continually on the alert and should use the drug with extra care in the presence of controlled infection and in infants at risk of infection.

5.3 Platelet Aggregation

NeoProfen, like other non-steroidal anti-inflammatory agents, can inhibit platelet aggregation. Preterm infants should be observed for signs of bleeding. Ibuprofen has been shown to prolong bleeding time (but within the normal range) in normal adult subjects. This effect may be exaggerated in patients with underlying hemostatic defects (see CONTRAINDICATIONS).

5.4 Bilirubin Displacement

Ibuprofen has been shown to displace bilirubin from albumin binding-sites; therefore, it should be used with caution in patients with elevated total bilirubin.

5.5 Administration

NeoProfen should be administered carefully to avoid extravascular injection or leakage, as solution may be irritating to tissue.

5.6 Serious Skin Reactions

NSAIDS, including ibuprofen, can cause serious skin reactions such as exfoliative dermatitis, Stevens-Johnson syndrome (SJS), toxic epidermal necrolysis (TEN), and acute generalized exanthematous pustulosis (AGEP), which can be fatal. Ibuprofen should be discontinued at the first appearance of skin rash or any other sign of hypersensitivity.

6 ADVERSE REACTIONS

6.1 Clinical Trials Experience

The most frequently reported adverse events with NeoProfen were as shown in Table 1.

Table 1. Adverse Events within 30 Days of Therapy in the Multicenter Study*
Adverse Event | % Incidence
Adverse Event | NeoProfen | Placebo
Sepsis | 43 | 37
Anemia | 32 | 25
Total Bleeding** | 32 | 29
Intraventricular Hemorrhage, Grades 1/2 | 15 | 13
Intraventricular Hemorrhage, Grades 3/4 | 15 | 10
Other Bleeding | 6 | 13
Intraventricular Hemorrhage, All Grades | 29 | 24
Apnea | 28 | 26
Gastrointestinal Disorders | 22 | 18
non-Necrotizing Enterocolitis
Total Renal Events** | 21 | 15
Renal Failure | 1 | 3
Renal Insufficiency, Impairment | 6 | 4
Urine Output Reduced | 3 | 1
Blood Creatinine Increased | 3 | 1
Blood Urea Increased with Hematuria | 1 | 1
Blood Urea Increased | 7 | 4
Respiratory Infection | 19 | 13
Skin Lesion/Irritation | 16 | 6
Hypoglycemia | 12 | 6
Hypocalcemia | 12 | 9
Respiratory Failure | 10 | 4
Urinary Tract Infection | 9 | 4
Adrenal Insufficiency | 7 | 1
Hypernatremia | 7 | 4
Edema | 4 | 0
Atelectasis | 4 | 1
* Within 30 days of therapy, with an event rate greater on NeoProfen than on placebo, and greater than 2 events on NeoProfen.
** A given subject may have experienced more than one specific event within these adverse event categories. Only the most severe grade of IVH counted for a given subject.

6.2 Renal Function

Compared to placebo, there was a small decrease in urinary output in the ibuprofen group on days 2-6 of life, with a compensatory increase in urine output on day 9. In other studies, adverse events classified as renal insufficiency including oliguria, elevated BUN, elevated creatinine, or renal failure were reported in ibuprofen treated infants.

6.3 Additional Adverse Events

The adverse events reported in the multicenter study and of unknown association include tachycardia, cardiac failure, abdominal distension, gastroesophageal reflux, gastritis, ileus, inguinal hernia, injection site reactions, cholestasis, various infections, feeding problems, convulsions, jaundice, hypotension, and various laboratory abnormalities including neutropenia, thrombocytopenia, and hyperglycemia.

6.4 Postmarketing Experience

Because these reactions are reported voluntarily from a population of uncertain size, it is not always possible to reliably estimate their frequency, or establish a causal relationship to drug exposure. The following adverse reactions have been identified from spontaneous post-marketing reports or published literature: gastrointestinal perforation, necrotizing enterocolitis, drug reaction with eosinophilia and systemic symptoms (DRESS), and pulmonary hypertension.

7 DRUG INTERACTIONS

- Diuretics: Ibuprofen may reduce the effect of diuretics; diuretics can increase the risk of nephrotoxicity of NSAIDs in dehydrated patients. Monitor renal function in patients receiving concomitant diuretics.
- Amikacin: Ibuprofen may decrease the clearance of amikacin.

8 USE IN SPECIFIC POPULATIONS

8.4 Pediatric Use

Safety and effectiveness have only been established in premature infants.

10 OVERDOSAGE

The following signs and symptoms have occurred in individuals (not necessarily in premature infants) following an overdose of oral ibuprofen: breathing difficulties, coma, drowsiness, irregular heartbeat, kidney failure, low blood pressure, seizures, and vomiting. There are no specific measures to treat acute overdosage with NeoProfen. The patient should be followed for several days because gastrointestinal ulceration and hemorrhage may occur.

11 DESCRIPTION

NeoProfen® is a clear sterile preservative-free solution of the L-lysine salt of (±)-ibuprofen which is the active ingredient. (±)-Ibuprofen is a nonsteroidal anti-inflammatory agent (NSAID). L-lysine is used to create a water-soluble drug product salt suitable for intravenous administration. Each mL of NeoProfen contains 17.1 mg of ibuprofen lysine (equivalent to 10 mg of (±)-ibuprofen) in Water for Injection, USP. The pH is adjusted to 7.0 with sodium hydroxide or hydrochloric acid.

The structural formula is:

NeoProfen is designated chemically as α-methyl-4-(2-methyl propyl) benzeneacetic acid lysine salt. Its molecular weight is 352.48. Its empirical formula is C19H32N2O4. It occurs as a white crystalline solid which is soluble in water and slightly soluble in ethanol.

12 CLINICAL PHARMACOLOGY

12.1 Mechanism of Action

The mechanism of action through which ibuprofen causes closure of a patent ductus arteriosus (PDA) in neonates is not known. In adults, ibuprofen is an inhibitor of prostaglandin synthesis.

12.2 Pharmacokinetics and Bioavailability Studies

The pharmacokinetic data were obtained from 54 NeoProfen-treated premature infants included in a double-blind, placebo-controlled, randomized, multicenter study. Infants were less than 30 weeks gestational age, weighed between 500 and 1000 g, and exhibited asymptomatic PDA with evidence of echocardiographic documentation of ductal shunting. Dosing was initially 10 mg/kg followed by 5 mg/kg at 24 and 48 hours.

The population average clearance and volume of distribution values of racemic ibuprofen for premature infants at birth were 3 mL/kg/h and 320 mL/kg, respectively. Clearance increased rapidly with post-natal age (an average increase of approximately 0.5 mL/kg/h per day). Inter-individual variability in clearance and volume of distribution were 55% and 14%, respectively. In general, the half-life in infants is more than 10 times longer than in adults.

The metabolism and excretion of ibuprofen in premature infants have not been studied.

In adults, renal elimination of unchanged ibuprofen accounts for only 10-15% of the dose. The excretion of ibuprofen and metabolites occurs rapidly in both urine and feces. Approximately 80% of the dose administered orally is recovered in urine as hydroxyl and carboxyl metabolites, respectively, as a mixture of conjugated and unconjugated forms. Ibuprofen is eliminated primarily by metabolism in the liver where CYP2C9 mediates the 2- and 3-hydroxylations of R- and S-ibuprofen. Ibuprofen and its metabolites are further conjugated to acyl glucuronides.

In neonates, renal function and the enzymes associated with drug metabolism are underdeveloped at birth and substantially increase in the days after birth.

14 CLINICAL STUDIES

In a double-blind, multicenter clinical study premature infants of birth weight between 500 and 1000 g, less than 30 weeks post-conceptional age, and with echocardiographic evidence of a PDA were randomized to placebo or NeoProfen. These infants were asymptomatic from their PDA at the time of enrollment. The primary efficacy parameter was the need for rescue therapy (indomethacin, open-label ibuprofen, or surgery) to treat a hemodynamically significant PDA by study day 14. An infant was rescued if there was clinical evidence of a hemodynamically significant PDA that was echocardiographically confirmed. A hemodynamically significant PDA was defined by three of the following five criteria ― bounding pulse, hyperdynamic precordium, pulmonary edema, increased cardiac silhouette, or systolic murmur ― or hemodynamically significant ductus as determined by a neonatologist.

One hundred and thirty-six premature infants received either placebo or NeoProfen (10 mg/kg on the first dose and 5 mg/kg at 24 and 48 hours). Mean birth age was 1.5 days (range: 4.6 – 73.0 hours), mean gestational age was 26 weeks (range: 23 – 30 weeks), and mean weight was 798 g (range: 530 – 1015 g). All infants had a documented PDA with evidence of ductal shunting. As shown in Table 2, 25% of infants on NeoProfen required rescue therapy versus 48% of infants on placebo (p=0.003 from logistic regression controlling for site).

Table 2. Summary of Efficacy Results, n (%)
 | NeoProfen | Placebo
 | N=68 | N=68
Required rescue through study day 14
Total | 17 (25) | 33 (48)
By age at treatment
Birth to < 24 hours | 3/14 (21) | 8/16 (50)
24-48 hours | 9/32 (28) | 16/37 (43)
> 48 hours | 5/22 (23) | 9/15 (60)
Echocardiographically proven PDA prior to rescue | 17 (100) | 32 (97)
Reasons for Rescue
Hemodynamically significant PDA per neonatologist | 14 (82) | 25 (76)
Bounding pulse | 6 (35) | 12 (36)
Systolic murmur | 6 (35) | 15 (45)
Pulmonary Edema | 3 (18) | 5 (15)
Hyperdynamic precordium | 2 (12) | 3 (9)
Increased cardiac silhouette | 1 (6) | 5 (15)

Of the infants requiring rescue within the first 14 days after the first dose of study drug, no statistically significant difference was observed between the NeoProfen and placebo groups for mean age at start of first rescue treatment (8.7 days, range 4-15 days, for the NeoProfen group and 6.9 days, range 2-15 days, for the placebo group).

The groups were similar in the number of deaths by day 14, the number of patients on a ventilator or requiring oxygenation at day 1, 4 and 14, the number of patients requiring surgical ligation of their PDA (12%), the number of cases of Pulmonary Hemorrhage and Pulmonary Hypertension by day 14, and Bronchopulmonary Dysplasia at day 28. In addition, no significant differences were noted in the incidences of Stage 2 and 3 Necrotizing Enterocolitis, Grades 3 and 4 Intraventricular Hemorrhage, Periventricular Leukomalacia and Retinopathy of Prematurity between groups as determined at 36±1 weeks adjusted gestational age.

Two supportive studies also determined that ibuprofen, either prophylactically (n=433, weight range: 400 – 2165 g) or as treatment (n=210, weight range: 400 – 2370 g), was superior to placebo (or no treatment) in preventing the need for rescue therapy for a symptomatic PDA.

16 HOW SUPPLIED/STORAGE AND HANDLING

How Supplied

NeoProfen (ibuprofen lysine) Injection is dispensed in treated [NeoProfen (ibuprofen lysine) Injection is dispensed in a glass vial having a silicon dioxide coating or polymer coating that inhibits the formation of particulates that result from the interaction of the ibuprofen lysine with untreated glass.] clear glass single-use vials, each containing 2 mL of sterile solution (NDC 55292-122-52). The solution is not buffered and contains no preservatives. Each milliliter contains 17.1 mg/mL (±)-ibuprofen L-lysine [equivalent to 10 mg/mL (±)-ibuprofen] dissolved in Water for Injection, USP. NeoProfen is supplied in a carton containing 3 single-use vials.

Storage and Handling

Store at 20 – 25°C (68 – 77°F); excursions permitted 15 – 30°C (59 – 86°F) [see USP Controlled Room Temperature]. Protect from light. Store vials in carton until contents have been used.

17 PATIENT COUNSELING INFORMATION

Infection

NeoProfen may alter signs of infection. Patients' caregivers should be informed to monitor the infant for any signs of infection.

Platelet Aggregation

Patients' caregivers should be informed that like other NSAIDS, NeoProfen can inhibit clot formation therefore their infant should be monitored for any signs of bleeding.

Administration

Patients' caregivers should be informed that the infants' skin and tissues should be monitored as leakage from administration may be irritating to tissue.

Manufactured by: Alcami Carolinas Corporation, Charleston, SC 29405, U.S.A.

For: Recordati Rare Diseases Inc., Bridgewater, NJ 08807, U.S.A.

® Trademark of Recordati Rare Diseases Inc.

Revised: 04/2024

PRINCIPAL DISPLAY PANEL - 2 mL Vial Carton

NDC 55292-122-52
3 x 2 mL Single Dose Vials

NeoProfen®
(ibuprofen lysine) injection

20mg/2mL
(10mg/mL)

Sterile Solution for
Intravenous Use Only

RECORDATI
RARE DISEASES
GROUP

Rx only